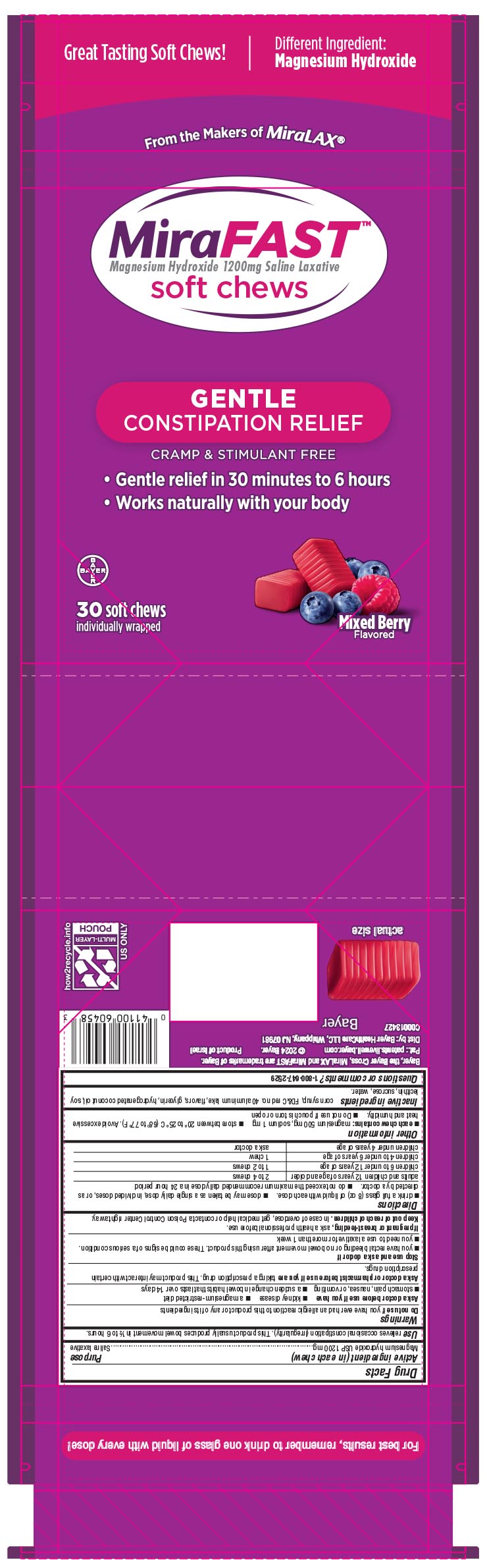 DRUG LABEL: MiraFAST soft chews
NDC: 11523-0159 | Form: BAR, CHEWABLE
Manufacturer: Bayer HealthCare LLC.
Category: otc | Type: HUMAN OTC DRUG LABEL
Date: 20250130

ACTIVE INGREDIENTS: MAGNESIUM HYDROXIDE 1200 mg/1 1
INACTIVE INGREDIENTS: FD&C RED NO. 40; GLYCERIN; CORN SYRUP; HYDROGENATED COCONUT OIL; LECITHIN, SOYBEAN; SUCROSE; WATER

MiraFAST soft chews UI1615762

Active ingredients (in each tablet)

Magnesium hydroxide USP 1200mg

Purpose

Saline laxative

Uses

relieves occasional constipation (irregularity). This product usually produces bowel movement in 1/2 to 6 hours.

Warnings

Do not use if you have ever had an allergic reaction to this product or any of its ingredients

Ask a doctor before use if you have

- kidney disease
- a magnesium-restricted diet
- stomach pain, nausea, or vomiting
- a sudden change in bowel habits that lasts over 14 days

Ask a doctor or pharmacist before use if you are taking a prescription drug.
This product may interact with certain prescription drugs.

Stop use and ask a doctor if

- you have rectal bleeding or no bowel movement after using this product. These could be signs of a serious condition.
- you need to use a laxative for more than 1 week

If pregnant or breast-feeding, ask a health professional before use.
Keep out of reach of children. In case of overdose, get medical help or contact a Poison Control Center right away.

Keep out of reach of children

Directions

- drink a full glass (8 oz) of liquid with each dose.
- dose may be taken as a single daily dose, in divided doses, or as directed by a doctor.
- do not exceed the maximum recommended daily dose in a 24 hour period

adults and children 12 years of age and over | 2 to 4 chews
children 6 to under 12 years of age | 1 to 2 chews
children 4 to 6 years of age | 1 chew
children under 4 years of age | ask a doctor

Other information

- each chew contains: magnesium 500mg, sodium 1mg
- store between 20o to 25o C (68o to 77o F). Avoid excessive heat and humidity.
- Do not use if pouch is torn or open

Inactive ingredients

corn syrup, FD&C red no. 40 aluminum lake, flavors, glycerin, hydrogenated coconut oil, soy lecithin, sucrose, water.

Questions or comments? 1-800-647-2529